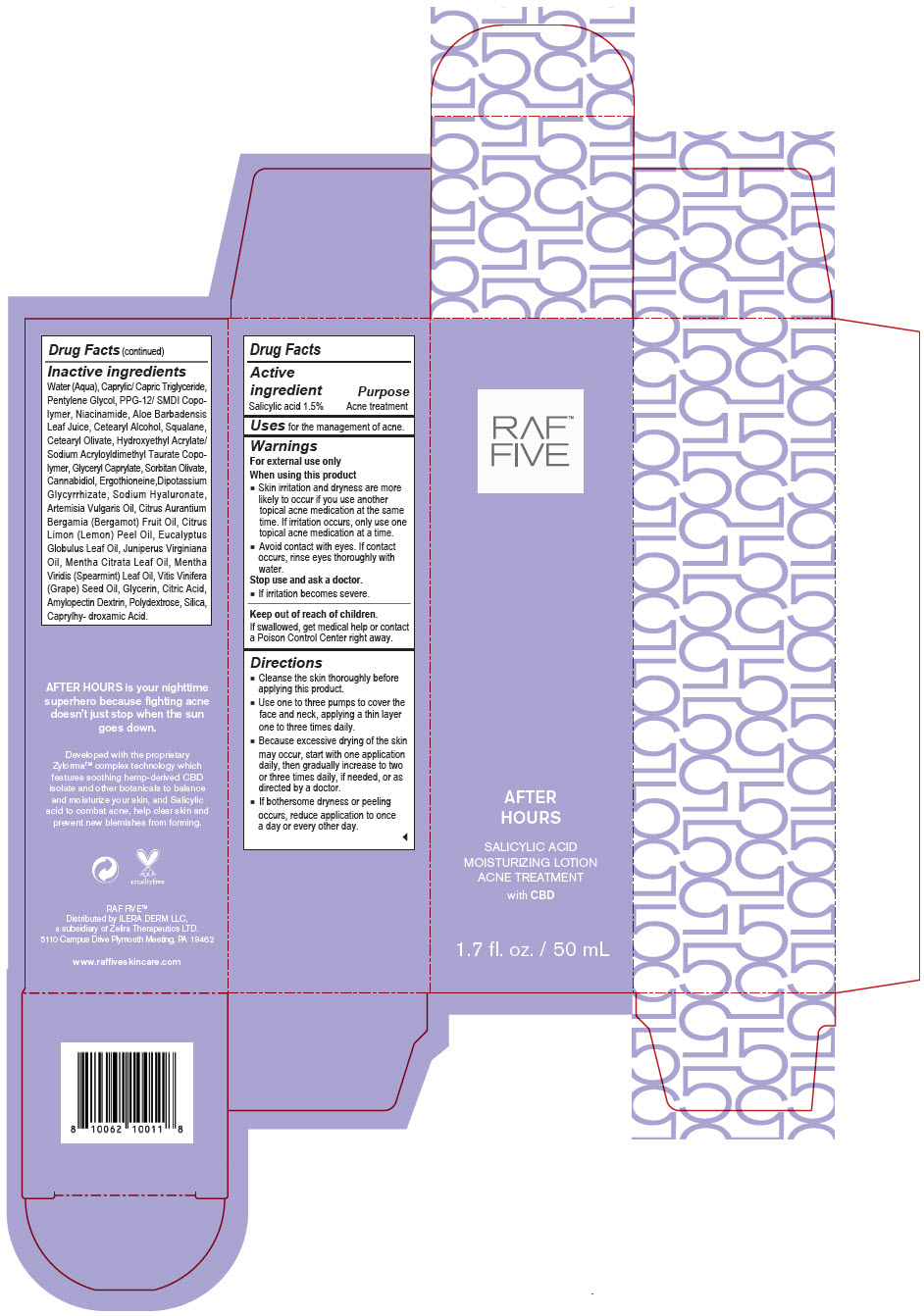 DRUG LABEL: RAF Five - After Hours Salicylic Acid Moisturizing
NDC: 66163-4454 | Form: LOTION
Manufacturer: Cosmetic Solutions LLC
Category: otc | Type: HUMAN OTC DRUG LABEL
Date: 20210826

ACTIVE INGREDIENTS: salicylic acid 1.5 g/100 mL
INACTIVE INGREDIENTS: Water; Medium-Chain Triglycerides; Pentylene Glycol; PPG-12/SMDI Copolymer; Niacinamide; Aloe Vera Leaf; Cetostearyl Alcohol; Squalane; Cetearyl Olivate; HYDROXYETHYL ACRYLATE/SODIUM ACRYLOYLDIMETHYL TAURATE COPOLYMER (100000 MPA.S AT 1.5%); Glyceryl Monocaprylate; Sorbitan Olivate; Cannabidiol; Ergothioneine; Glycyrrhizinate Dipotassium; Hyaluronate Sodium; Artemisia Vulgaris Top Oil; Bergamot Oil; Lemon Oil, Cold Pressed; Eucalyptus Oil; Juniperus Virginiana Oil; Spearmint Oil; Grape Seed Oil; Glycerin; Citric Acid Monohydrate; Polydextrose; Silicon Dioxide; Caprylhydroxamic Acid

RAF™ Five - After Hours Salicylic Acid Moisturizing

Drug Facts

Active ingredient

Salicylic acid 1.5%

Purpose

Acne treatment

Uses

for the management of acne.

Warnings

For external use only

When using this product

- Skin irritation and dryness are more likely to occur if you use another topical acne medication at the same time. If irritation occurs, only use one topical acne medication at a time.
- Avoid contact with eyes. If contact occurs, rinse eyes thoroughly with water.

Stop use and ask a doctor.

- If irritation becomes severe.

Keep out of reach of children.

If swallowed, get medical help or contact a Poison Control Center right away.

Directions

- Cleanse the skin thoroughly before applying this product.
- Use one to three pumps to cover the face and neck, applying a thin layer one to three times daily.
- Because excessive drying of the skin may occur, start with one application daily, then gradually increase to two or three times daily, if needed, or as directed by a doctor.
- If bothersome dryness or peeling occurs, reduce application to once a day or every other day.

Inactive ingredients

Water (Aqua), Caprylic/ Capric Triglyceride, Pentylene Glycol, PPG-12/ SMDI Copolymer, Niacinamide, Aloe Barbadensis Leaf Juice, Cetearyl Alcohol, Squalane, Cetearyl Olivate, Hydroxyethyl Acrylate/ Sodium Acryloyldimethyl Taurate Copolymer, Glyceryl Caprylate, Sorbitan Olivate, Cannabidiol, Ergothioneine,Dipotassium Glycyrrhizate, Sodium Hyaluronate, Artemisia Vulgaris Oil, Citrus Aurantium Bergamia (Bergamot) Fruit Oil, Citrus Limon (Lemon) Peel Oil, Eucalyptus Globulus Leaf Oil, Juniperus Virginiana Oil, Mentha Citrata Leaf Oil, Mentha Viridis (Spearmint) Leaf Oil, Vitis Vinifera (Grape) Seed Oil, Glycerin, Citric Acid, Amylopectin Dextrin, Polydextrose, Silica, Caprylhy- droxamic Acid.

Distributed by ILERA DERM LLC,
a subsidiary of Zelira Therapeutics LTD.
5110 Campus Drive Plymouth Meeting, PA 19462

PRINCIPAL DISPLAY PANEL - 50 mL Bottle Carton

RAF™
FIVE

AFTER
HOURS

SALICYLIC ACID
MOISTURIZING LOTION
ACNE TREATMENT

with CBD

1.7 fl. oz. / 50 mL